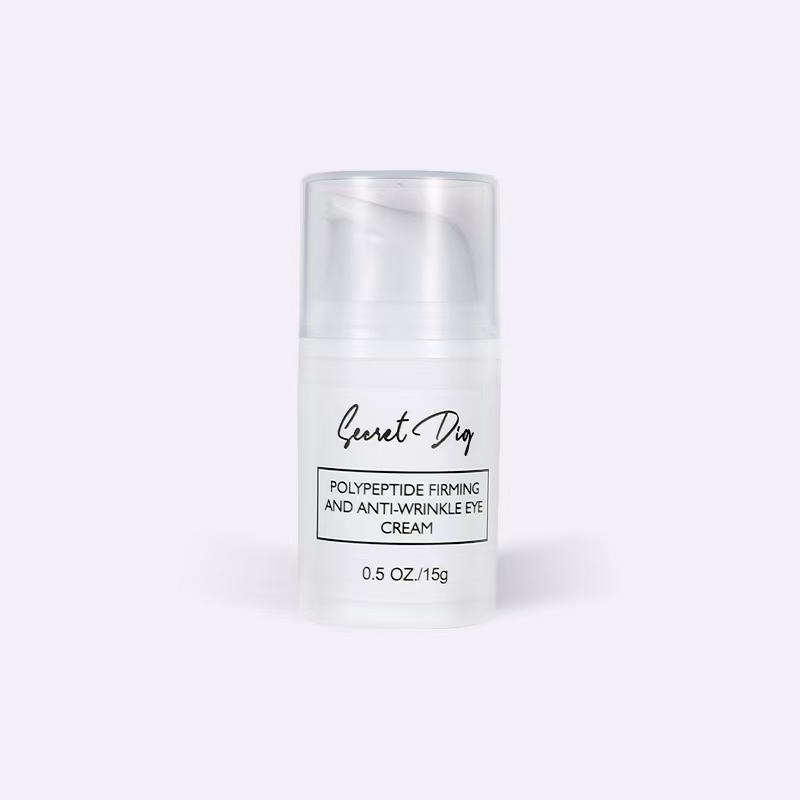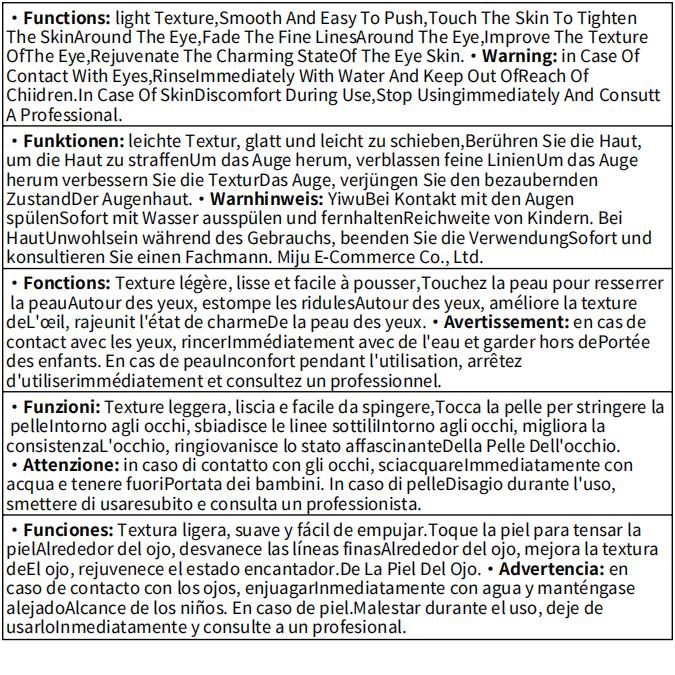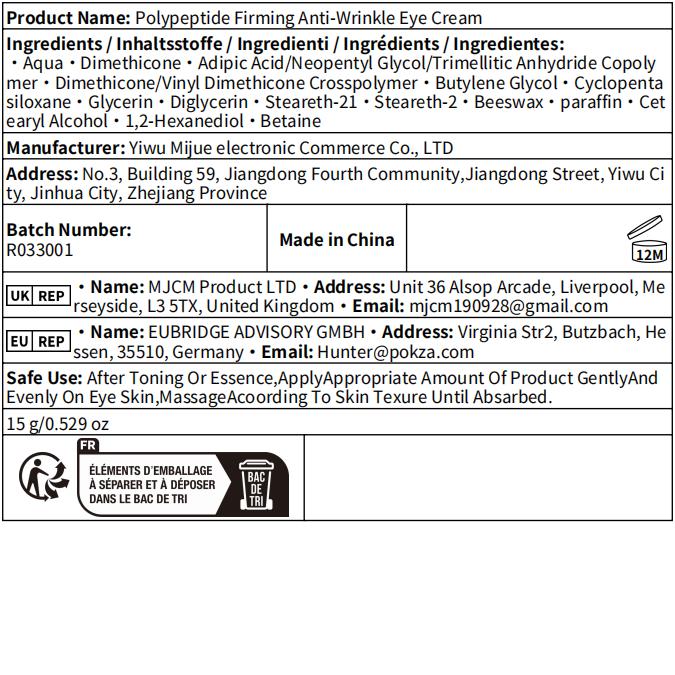 DRUG LABEL: Polypeptide Firming and Anti-Wrinkle Eye Cream
NDC: 84462-459 | Form: CREAM
Manufacturer: Yiwu Mijue electronic Commerce Co., LTD
Category: otc | Type: HUMAN OTC DRUG LABEL
Date: 20240828

ACTIVE INGREDIENTS: DIMETHICONE 19.8 g/100 g
INACTIVE INGREDIENTS: WATER; STEARETH-2; STEARETH-21; YELLOW WAX; GLYCERIN; ADIPIC ACID; CYCLOMETHICONE 5; 1,2-HEXANEDIOL; DIGLYCERIN; CETOSTEARYL ALCOHOL; DIMETHICONE/VINYL DIMETHICONE CROSSPOLYMER (HARD PARTICLE); PARAFFIN; BUTYLENE GLYCOL

84462-459 蜜掘电子

Active Ingredient

Dimethicone 19.8%

Purpose

The texture is light, smooth, and easy to apply. It tightens the skin around the eyes upon contact, reduces fine lines around the eyes, improves the texture of the skin around the eyes, and restores the charming appearance of the eye area.

Use

After using toner or essence, apply an appropriate amount of the product evenly to the skin around the eyes and gently massage along the skin's texture until absorbed.

Warnings

If the product accidentally comes into contact with the eyes, rinse immediately with clean water and keep out of reach of children. If skin discomfort occurs during use, please stop using it immediately and consult a professional.

Do not use if you have a known allergy to any of the ingredients.
Do not use on broken or irritated skin.
Do not use if the seal is broken or missing.

When Using

When using this product, avoid direct contact with the eyes.
When using this product, apply only to the intended area.
When using this product, use only as directed.

Stop Use

Stop use if irritation or rash occurs.
Stop use if skin discomfort persists.

Ask Doctor

Ask a doctor if you are unsure whether this product is right for you.
Ask a doctor before use if you have sensitive skin.

Keep Oot Of Reach Of Children

Keep out of reach of children to prevent accidental ingestion or misuse.If swallowed, get medical help or contact a Poison Control Center right away.

Directions

After cleansing, gently apply a small amount around the eyes.Use twice daily, morning and night.Gently massage until fully absorbed.

Other information

Store in a cool, dry place away from direct sunlight.

For external use only.

Do not freeze.

Inactive ingredients

Aqua 、Cyclopentasiloxane、Steareth-21、Steareth-2、Beeswax、Paraffin、Cetearyl Alcohol、1,2-Hexanediol、Glycerin、Butylene Glycol、Adipic Acid/Neopentyl Glycol/Trimellitic Anhydride Copolymer、Diglycerin、